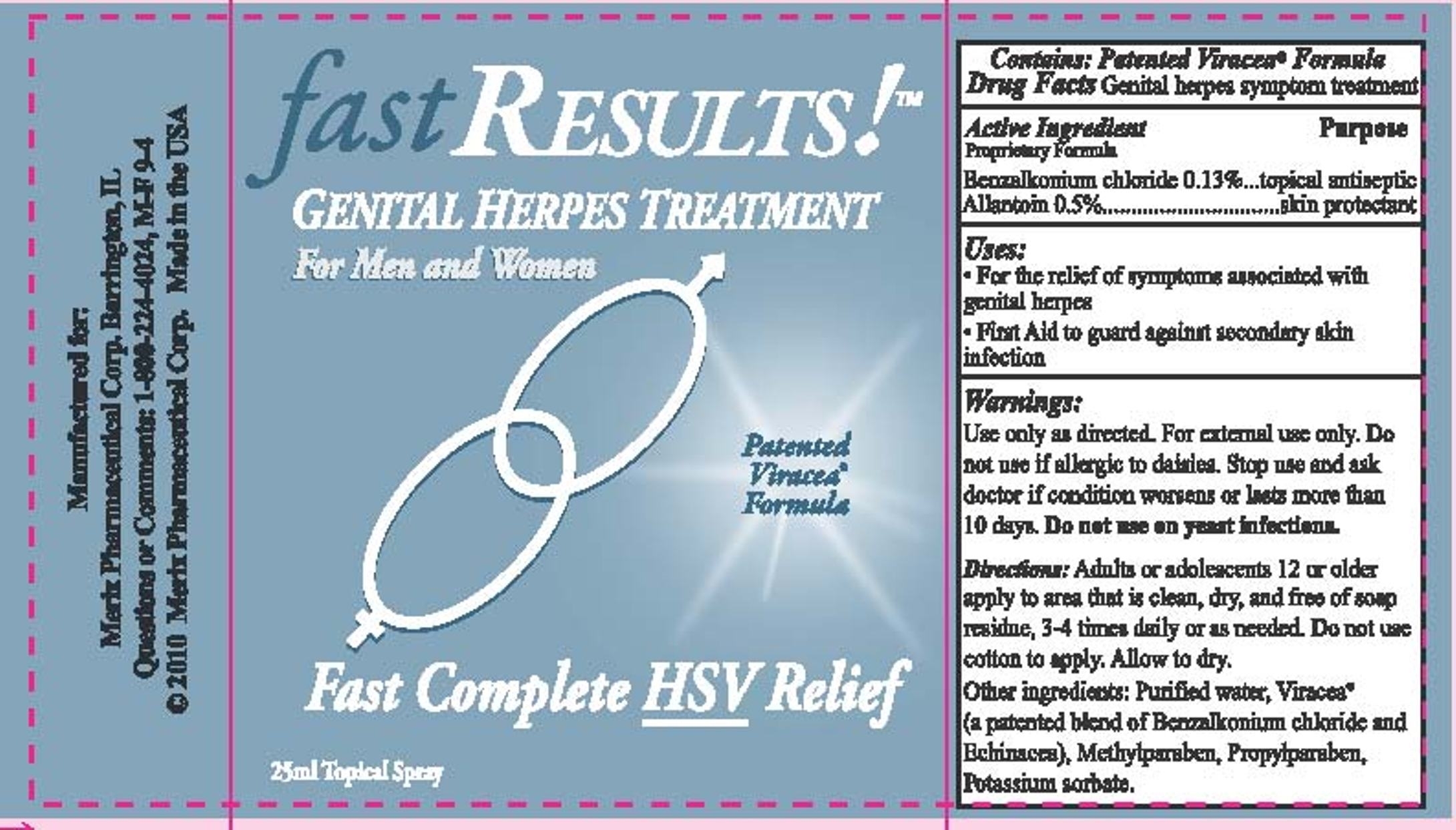 DRUG LABEL: Fast Results Genital Herpes Treatment
NDC: 63287-425 | Form: LIQUID
Manufacturer: Merix Pharmaceutical Corp.
Category: otc | Type: HUMAN OTC DRUG LABEL
Date: 20120522

ACTIVE INGREDIENTS: Benzalkonium Chloride 1.3 mL/1 mL; Allantoin 5 mL/1 mL
INACTIVE INGREDIENTS: Water; Methylparaben; Potassium Sorbate; Propylparaben; Echinacea purpurea flowering top

DRUGS FACTS

ACTIVE INGREDIENTS:

Benzalkonium chloride 0.13 %
Allantoin 0.5 %

USES:

For the relief of symptoms associated with genital herpes
First Aid to guard against secondary skin infection

WARNINGS:

Use only as directed. For external use only. Do not use if allergic to daisies.
Stop use and ask doctor if condition worsens or last more than 10 days.
Do not use on yeast infections.

KEEP OUT OF REACH OF CHILDREN:

Keep this and all drugs out of reach of children.
In case of accidental ingestion other then intended use, seek professional assistance
or call a poison control center.

DIRECTIONS:

Adults or adolescents 12 or older apply to clean dry area free of soap or cleanser residue.

DOSAGE AND ADMINISTRATION

Apply to area as need 3-4 times daily. Do no use cotton to apply.
Allow to dry.

Other Ingredients:

Purified water, Viracea (a patented blend of Bensalkonium chloride and Echinacea)
Methylparaben, Propylparaben, Potassium sorbate.

Fast Results label